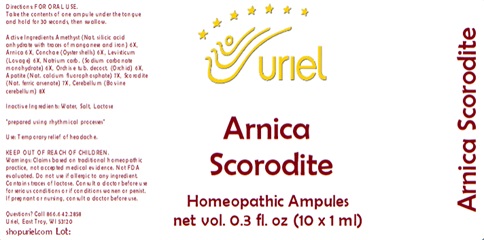 DRUG LABEL: Arnica Scorodite
NDC: 48951-1155 | Form: LIQUID
Manufacturer: Uriel Pharmacy Inc.
Category: homeopathic | Type: HUMAN OTC DRUG LABEL
Date: 20240206

ACTIVE INGREDIENTS: SILICON DIOXIDE 6 [hp_X]/1 mL; ARNICA MONTANA 6 [hp_X]/1 mL; OSTREA EDULIS SHELL 6 [hp_X]/1 mL; LEVISTICUM OFFICINALE ROOT 6 [hp_X]/1 mL; SODIUM CARBONATE 6 [hp_X]/1 mL; ORCHIS MASCULA TUBER 6 [hp_X]/1 mL; FLUORAPATITE 7 [hp_X]/1 mL; FERROUS ARSENATE 7 [hp_X]/1 mL; BOS TAURUS CEREBELLUM 8 [hp_X]/1 mL
INACTIVE INGREDIENTS: WATER; SODIUM CHLORIDE

Arnica Scorodite

INDICATIONS AND USAGE

Directions: FOR ORAL USE.

DOSAGE AND ADMINISTRATION

Take the contents of one ampule
under the tongue and hold for
30 seconds, then swallow.

ACTIVE INGREDIENT

Active Ingredients: Amethyst (Nat. silicic acid anhydrate with traces of manganese and iron) 6X, Arnica 6X, Conchae (Oyster shells) 6X, Levisticum (Lovage) 6X, Natrium carb. (Sodium carbonate monohydrate) 6X, Orchis e tub. decoct. (Orchid) 6X, Apatite (Nat. calcium fluorophosphate) 7X, Scorodite (Nat. ferric arsenate) 7X, Cerebellum (Bovine cerebellum) 8X

Inactive Ingredients: Water, Salt, Lactose

"prepared using rhythmical processes"

PURPOSE

Use: Temporary relief of headache.

KEEP OUT OF REACH OF CHILDREN.

WARNINGS

Warnings: Claims based on traditional homeopathic practice, not accepted medical evidence. Not FDA evaluated. Do not use if allergic to any ingredient. Contains traces of lactose. Consult a doctor before use for serious conditions or if conditions worsen or persist. If pregnant or nursing, consult a doctor before use.

Questions? Call 866.642.2858
Uriel, East Troy, WI 53120
shopuriel.com Lot: